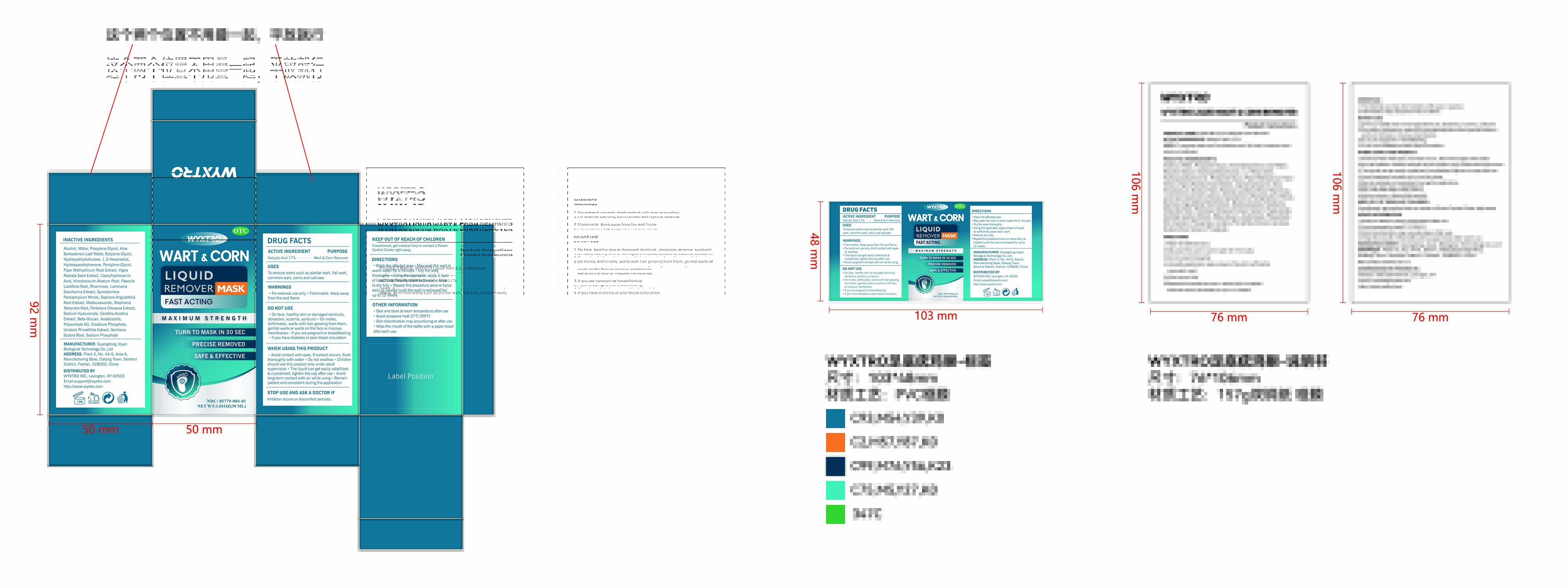 DRUG LABEL: WART CORN  Liquid  REMOVER Mask
NDC: 85779-004 | Form: LIQUID
Manufacturer: Guangdong Joyan Biological Technology Co.,Ltd
Category: otc | Type: HUMAN OTC DRUG LABEL
Date: 20260106

ACTIVE INGREDIENTS: SALICYLIC ACID 0.17 g/1 mL
INACTIVE INGREDIENTS: PENTYLENE GLYCOL; HYDROXYETHYLCELLULOSE; ASIATICOSIDE; PURSLANE; PAEONIA LACTIFLORA ROOT; SODIUM HYALURONATE; CAPRYLHYDROXAMIC ACID; PROPYLENE GLYCOL; SODIUM PHOSPHATE; STEPHANIA TETRANDRA ROOT; ALCOHOL; WATER; PIPER METHYSTICUM ROOT; CENTELLA ASIATICA TRITERPENOIDS; UNDARIA PINNATIFIDA; MUNG BEAN; SACCHARINA LATISSIMA THALLUS; SOPHORA FLAVESCENS ROOT; GENTIANA SCABRA ROOT; RHAMNOSE; ALOE VERA LEAF OIL; POLYSORBATE 60; TRANSFORMING GROWTH FACTOR BETA RECEPTOR TYPE 3; DISODIUM PHOSPHATE; VINCETOXICUM ATRATUM ROOT; HYDROXYACETOPHENONE; GYNOSTEMMA PENTAPHYLLUM WHOLE; MADECASSOSIDE; BUTYLENE GLYCOL; 1,2-HEXANEDIOL

85779-004 WART & CORN LIQUID REMOVER MASK

ACTIVE INGREDIENT

Salicylic acid 17%

PURPOSE

remove warts

INDICATIONS AND USAGE

To remove warts such as plantar wart, flatwart, common wart, corns and calluses.

WARNINGS

Flammable. Keep away from fire and flame.
For external use only, don't contact with eyes or swallow.
The liquid can get easily volatilized & crystallized, tighten the cap after use.
Avoid long-term contact with air while using

DO NOT USE

On face, healthy skin or damaged skin(cuts, abrasions, eczema, sunburn).
On moles, birthmarks, warts with hair growing from them, genital warts or warts on the face or mucous membranes.
lf you are pregnant or breastfeeding.
if you have diabetes or poor blood circulation.

WHEN USING

.Seal and store after use.
Stop use and ask a doctor if discomfort persists.
Children should use it under the supervision of adults.
Remain patient and consistent during theapplication.

Stop use and ask a doctor if discomfort persists.

KEEP OUT OF REACH OF CHILDREN

lf swallowed, get medical help or contact a Poison Control Center(1-800-222-1222) right away.

DOSAGE AND ADMINISTRATION

Wash the affected area.
May soak the wart in warm water for 5 minutes.
Dry the area thoroughly.
Using the applicator, apply a layer of liquid to sufficiently cover each wart.
Allow to dry fully.
Repeat this procedure once or twice daily as needed (until the wart is removed) for up to 12 weeks.

INACTIVE INGREDIENT

ALCOHOL
WATER
PROPYLENE GLYCOL
ALOE BARBADENSIS LEAF WATER
BUTYLENE GLYCOL
HYDROXYETHYLCELLULOSE
1,2-HEXANEDIOL
HYDROXYACETOPHENONE
PENTYLENE GLYCOL
PIPER METHYSTICUM ROOT EXTRACT
VIGNA RADIATA SEED EXTRACT
CAPRYLHYDROXAMIC ACID
VINCETOXICUM ATRATUM ROOT
PAEONIA LACTIFLORA ROOT
RHAMNOSE
LAMINARIA SACCHARINA EXTRACT
GYNOSTEMMA PENTAPHYLLUM WHOLE
SOPHORA ANGUSTIFOLIA ROOT EXTRACT
MADECASSOSIDE
STEPHANIA TETRANDRA ROOT
PORTULACA OLERACEA EXTRACT
SODIUM HYALURONATE
CENTELLA ASIATICA EXTRACT
BETA-GLUCAN
ASIATICOSIDE
POLYSORBATE 60
DISODIUM PHOSPHATE
UNDARIA PINNATIFIDA EXTRACT
GENTIANA SCABRA ROOT
SODIUM PHOSPHATE